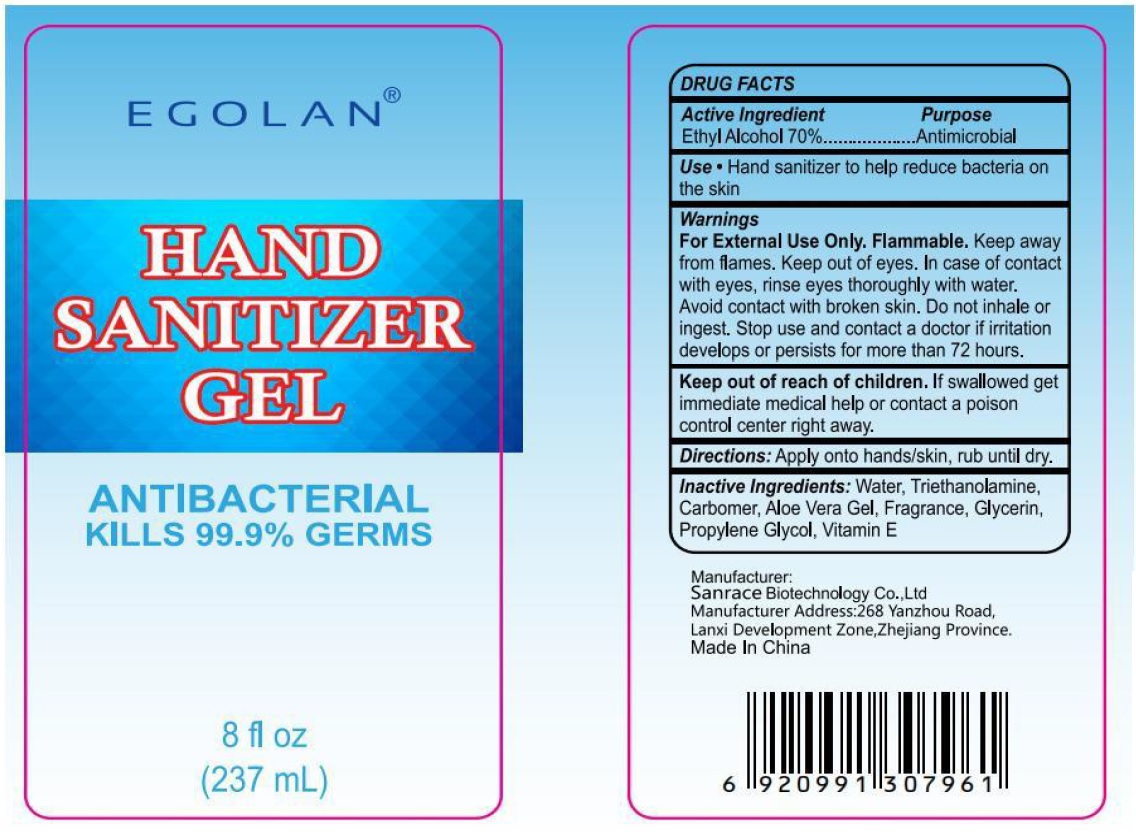 DRUG LABEL: EGOLAN HAND SANITIZER
NDC: 75448-025 | Form: GEL
Manufacturer: Sanrace Biotechnology Co., Ltd.
Category: otc | Type: HUMAN OTC DRUG LABEL
Date: 20200703

ACTIVE INGREDIENTS: ALCOHOL 70 mL/100 mL
INACTIVE INGREDIENTS: WATER; TROLAMINE; CARBOMER HOMOPOLYMER, UNSPECIFIED TYPE; ALOE VERA LEAF; GLYCERIN; PROPYLENE GLYCOL; .ALPHA.-TOCOPHEROL

EGOLAN® HAND SANITIZER GEL

Active Ingredient

Ethyl Alcohol 70%

Purpose

Antimicrobial

INDICATIONS AND USAGE

Use: Hand sanitizer to help reduce bacteria on the skin

Warnings

For External use only. Flammable. Keep away from flames. Keep out of eyes. In case of contact with eyes, rinse eyes thoroughly with water. Avoid contact with broken skin. Do not inhale or ingest. Stop use and contact doctor if irritation develops or persists for more than 72 hours.

Keep out of reach of children. If swallowed get immediate medical help or contact a poison control center right away.

DOSAGE AND ADMINISTRATION

Directions: Apply onto hands/skin, rub until dry.

INACTIVE INGREDIENT

Inactive Ingredients: Water, Triethanolamine, Carbomer, Aloe Vera Gel, Fragrance, Glycerin, Propylene Glycol, Vitamin E

ANTIBACTERIAL

KILLS 99.9% GERMS

Manufacturer:

Sanrace Biotechnology Co., Ltd

Manufacturer Address:268 Yanzhou Road,

Lanxi Development Zone,Zhejiang Province.

Made In China.